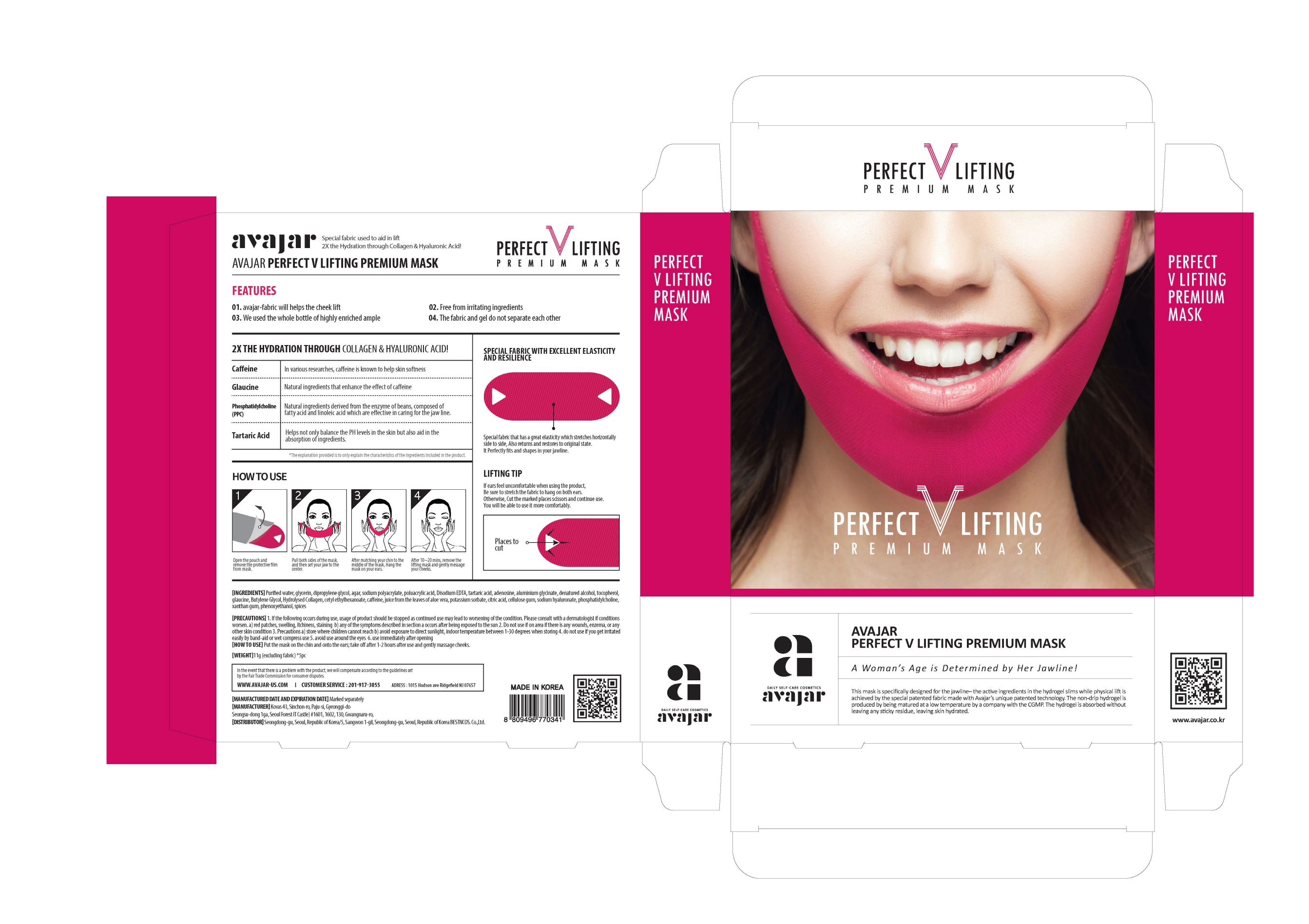 DRUG LABEL: Perfect V Lifting Premium Mask
NDC: 71224-0010 | Form: LIQUID
Manufacturer: AVAJAR CO LTD
Category: otc | Type: HUMAN OTC DRUG LABEL
Date: 20190618

ACTIVE INGREDIENTS: GLYCERIN 30 g/100 g
INACTIVE INGREDIENTS: GLAUCINE; WATER; CAFFEINE; TARTARIC ACID; ADENOSINE

Drug Facts

ACTIVE INGREDIENT

Glycerin

INACTIVE INGREDIENT

Water, Tartaric Acid, Glaucine, Caffeine, Aloe Barbadensis Leaf Juice,Sodium Hyaluronate, Phosphatidylcholine, etc.

PURPOSE

Skin protectant: Anti-Wrinkle, Lifting

keep out of reach of the children

INDICATIONS AND USAGE

1. Open pouch and remove the film.

2. Hold each ends of the mask with hands, STRETCH and place the middle on the chin.

3. After matching your chin to the middle of the mask, hook onto the ears.

4. After use, remove mask and lighly massage both cheeks.

DOSAGE AND ADMINISTRATION

for external use only

WARNINGS

1. If the following symptoms occur after product use, stop using the product immediately and consult a dermatologist (continuous use can exacerbate the symptoms).
1) Occurrence of red spots, swelling, itchiness, and other skin irritation
2) If the symptoms above occur after the application area is exposed to direct sunlight
2. Do not use on open wounds, eczema, and other skin irritations
3. Precaution for Storage and Handling
1) Close the lid after use
2) Keep out of reach of infants and children
3) Do not to store in a place with high/low temperature and exposed to direct sunlight